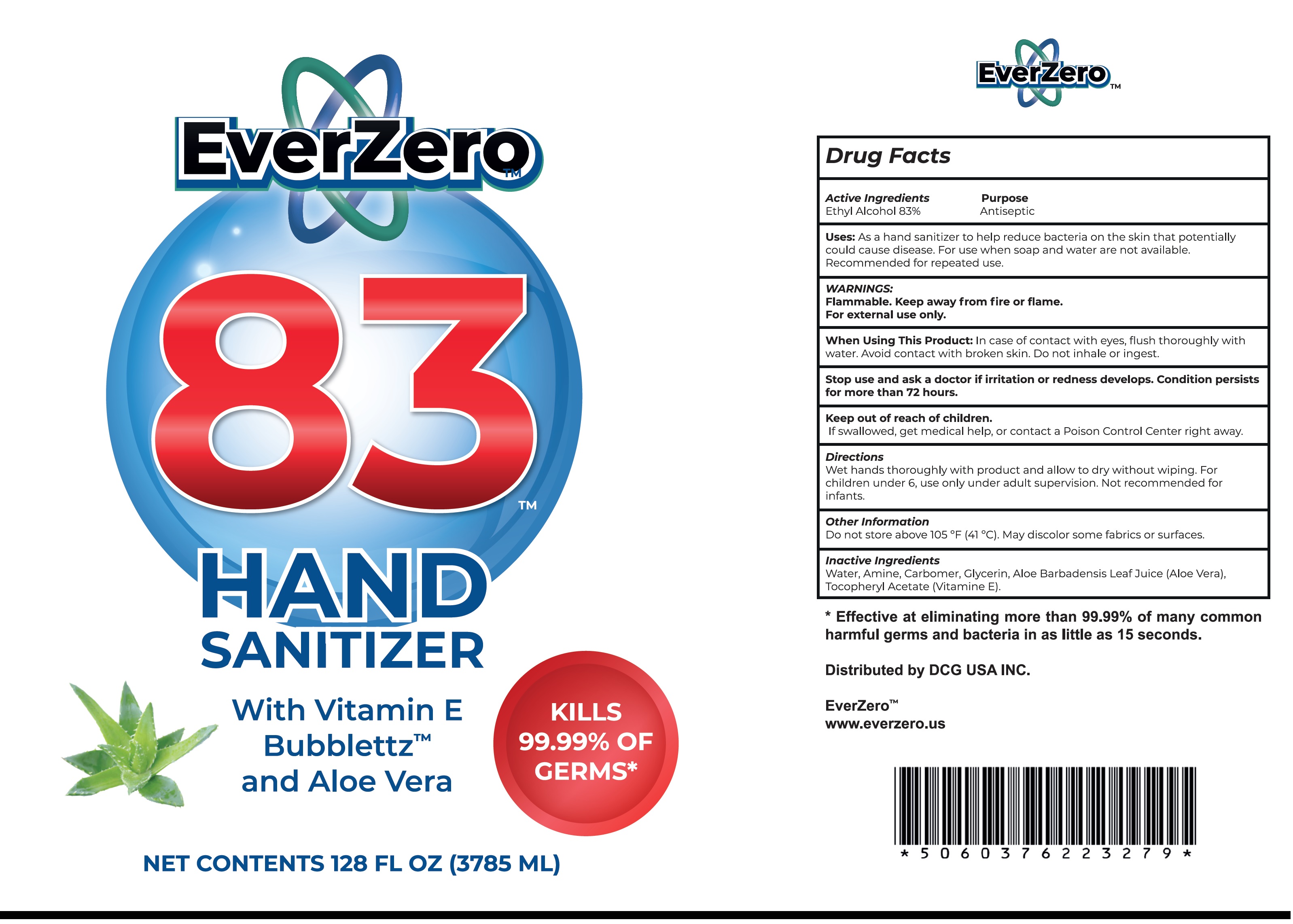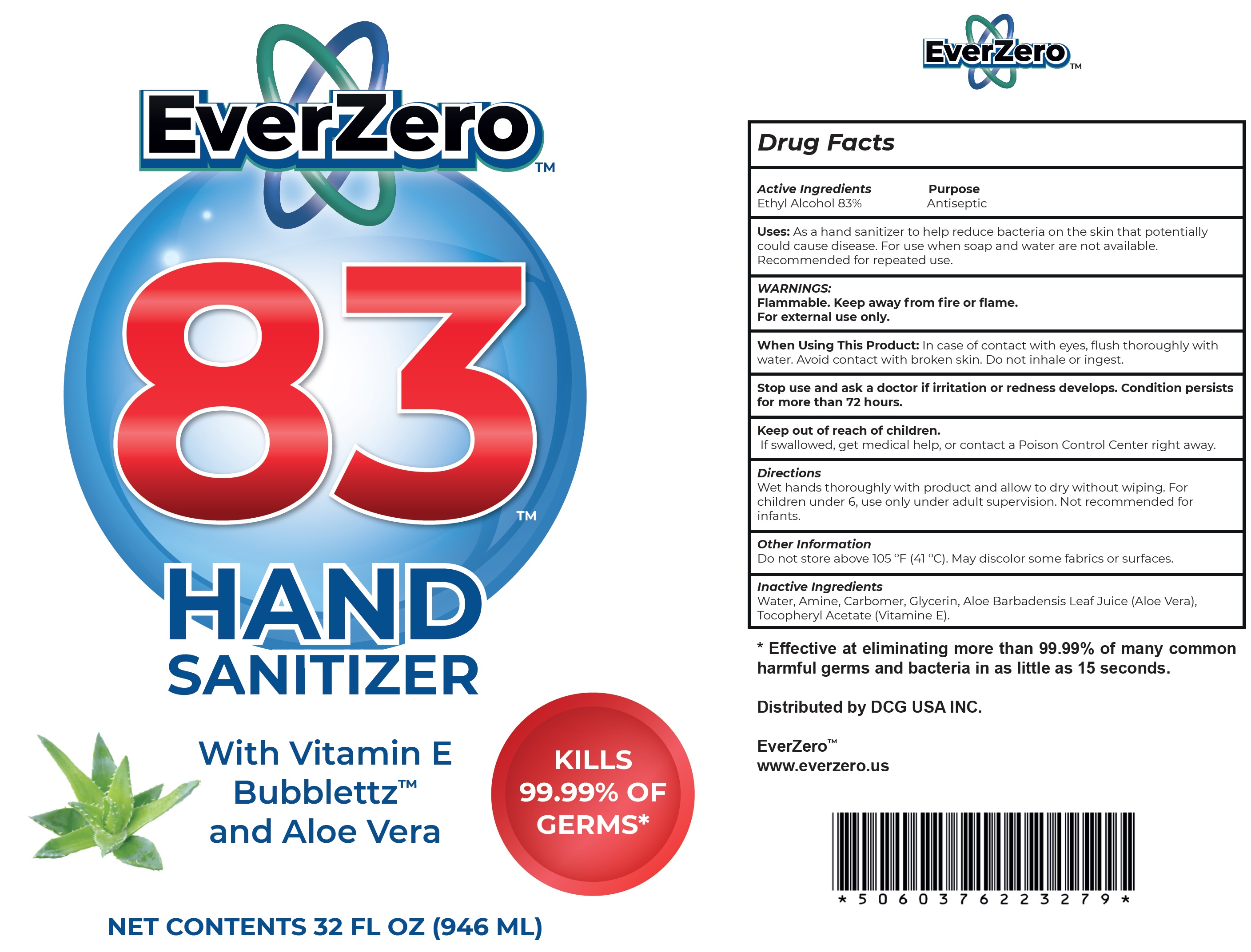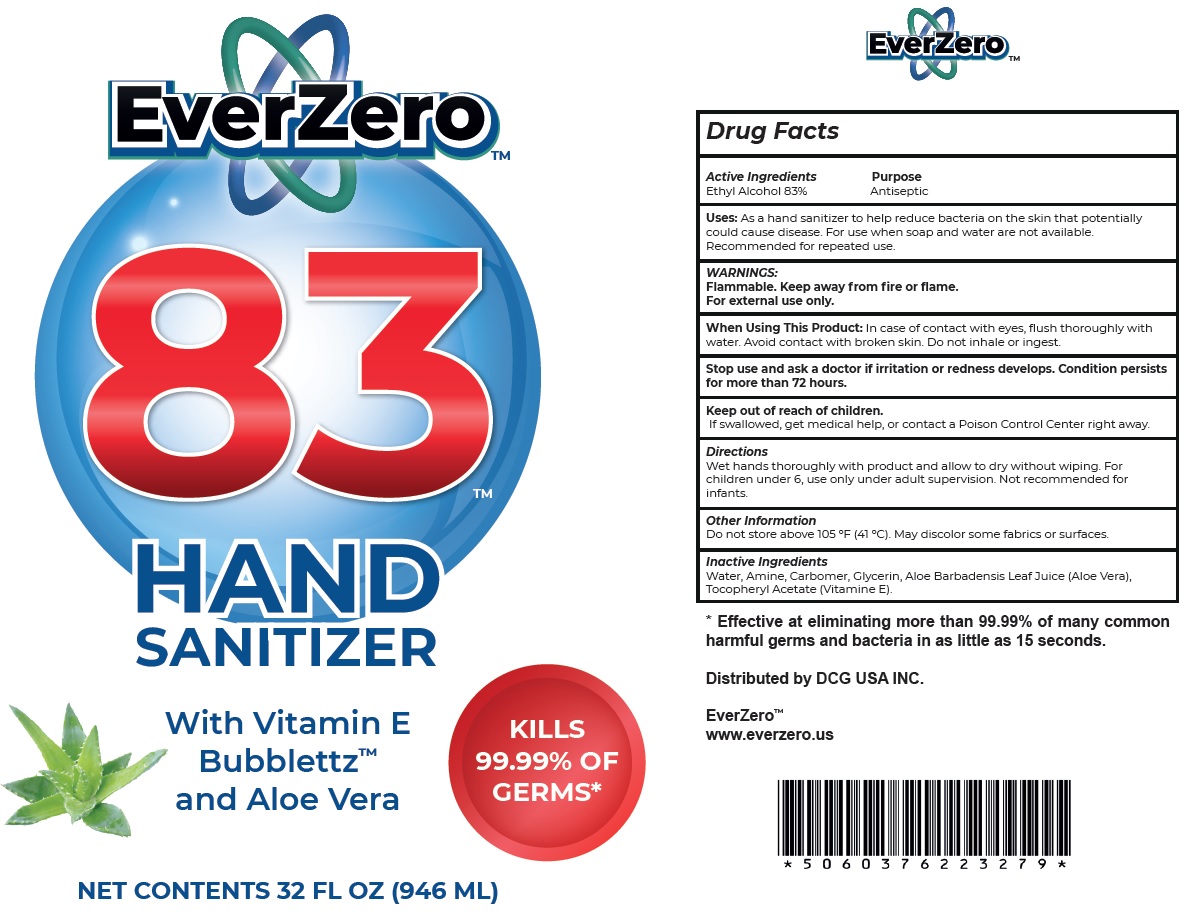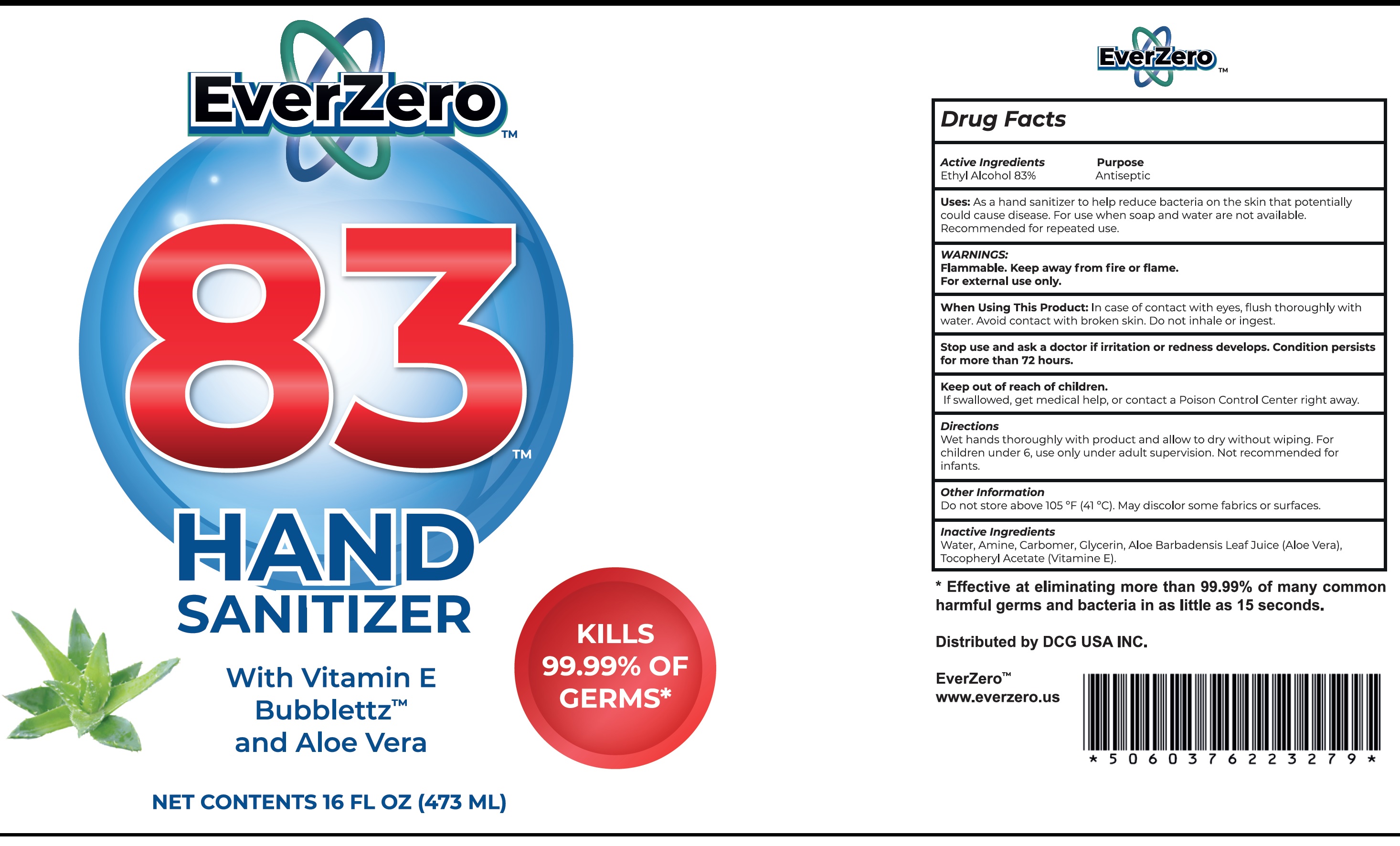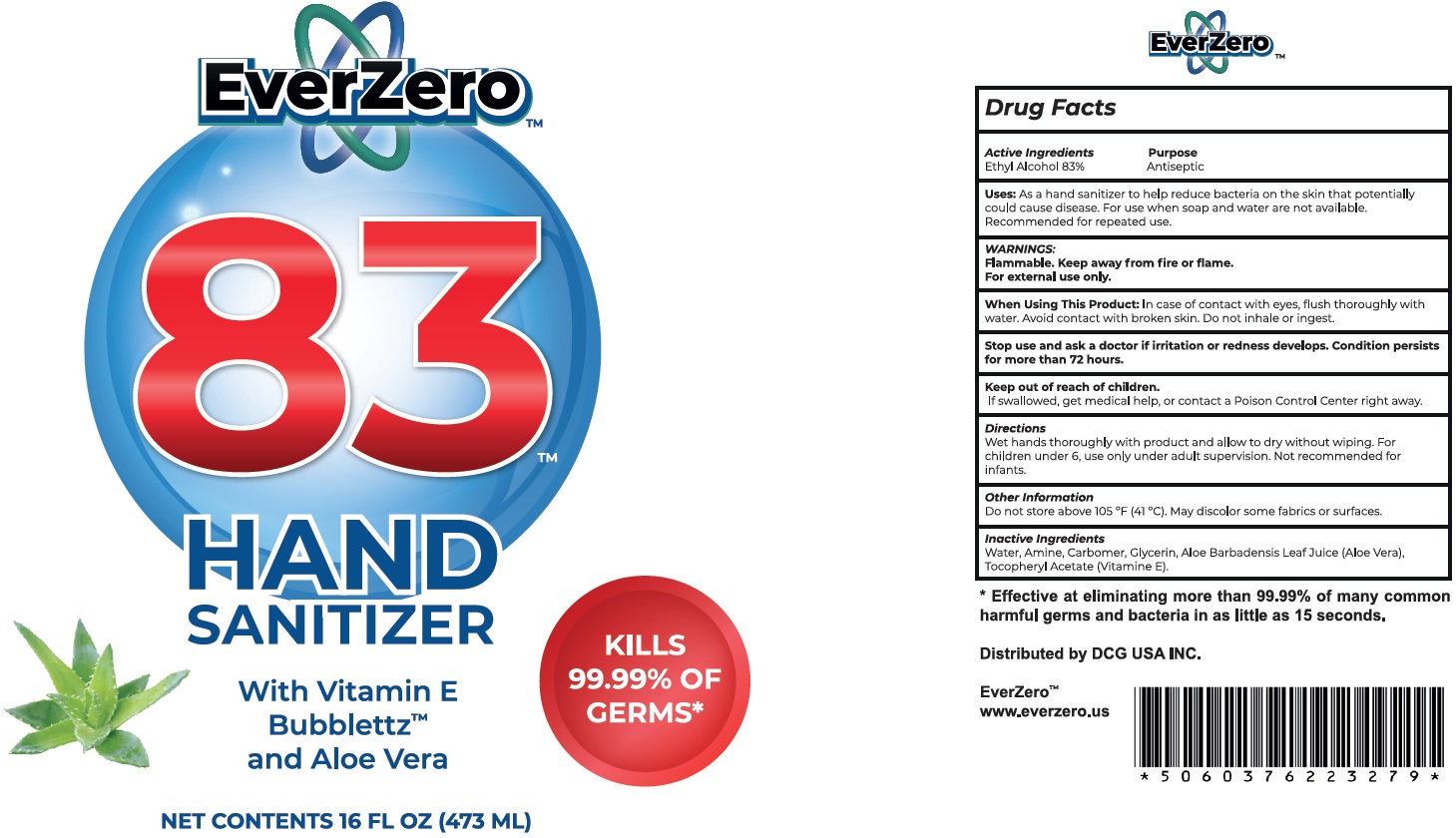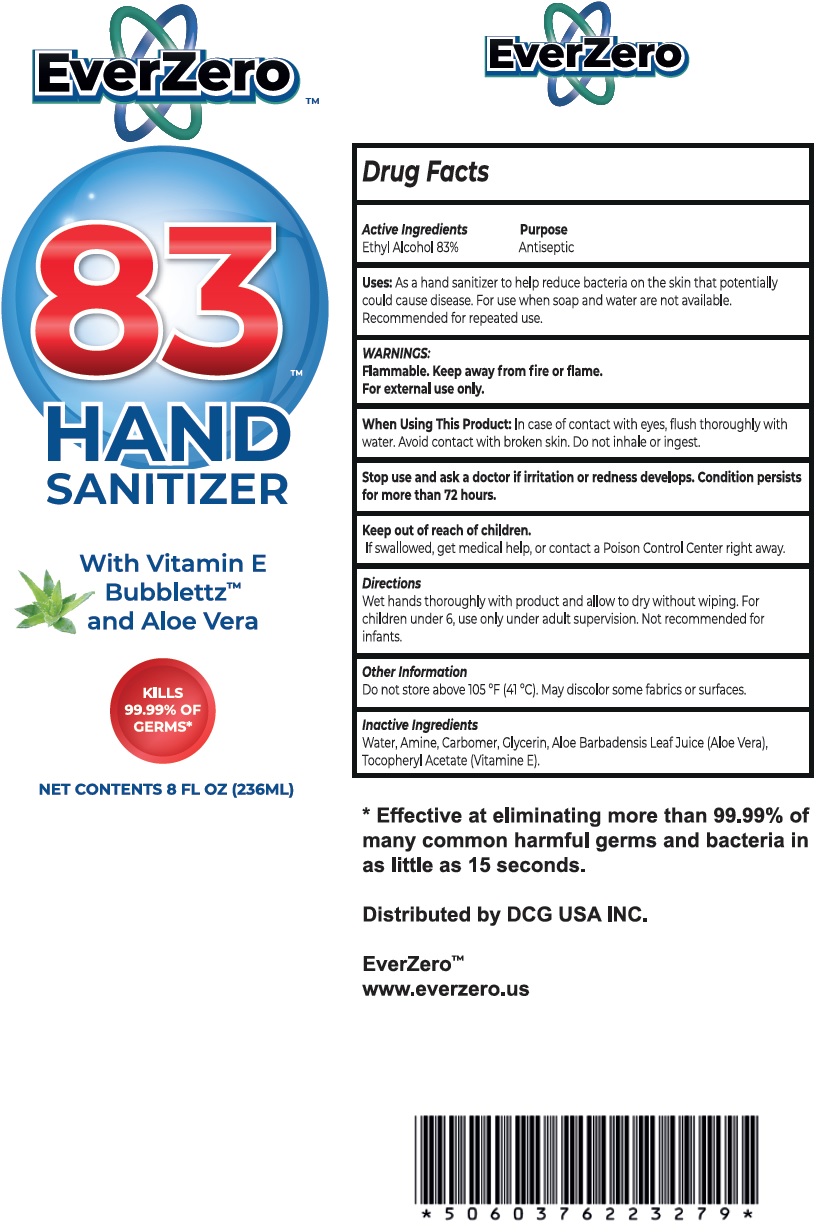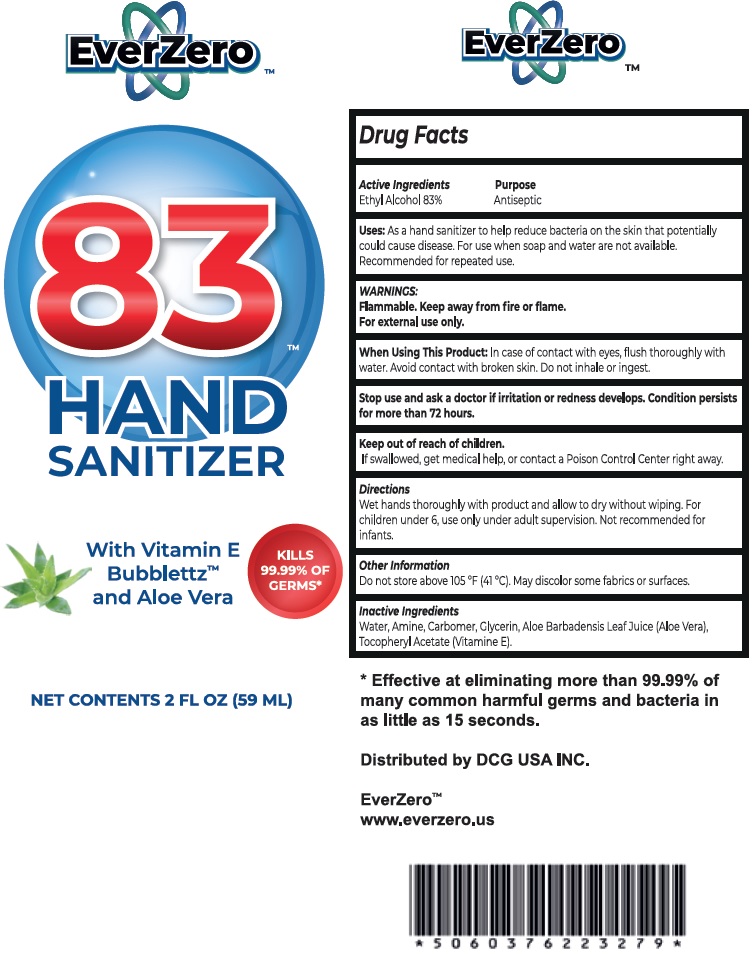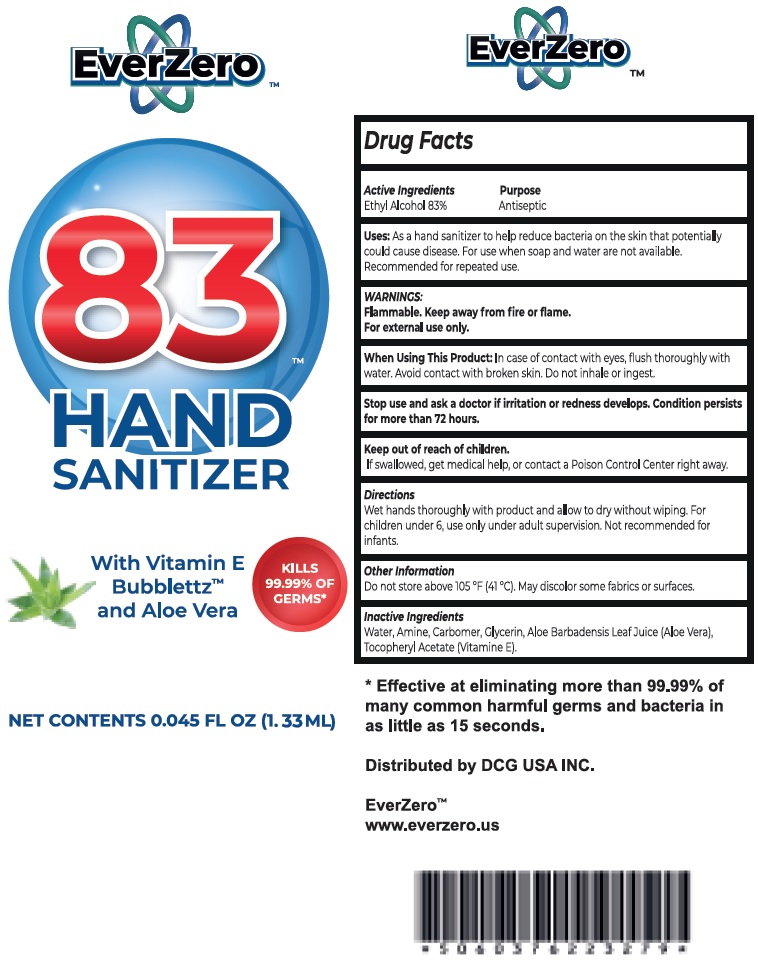 DRUG LABEL: EverZero 83 Hand Sanitizer with Vitamin E and Aloe Vera
NDC: 80944-000 | Form: GEL
Manufacturer: DCG USA, INC
Category: otc | Type: HUMAN OTC DRUG LABEL
Date: 20211202

ACTIVE INGREDIENTS: ALCOHOL 0.83 mL/1 mL
INACTIVE INGREDIENTS: WATER; CARBOMER HOMOPOLYMER, UNSPECIFIED TYPE; GLYCERIN; ALOE VERA LEAF; .ALPHA.-TOCOPHEROL ACETATE; AMINOMETHYLPROPANOL

EverZero 83 Hand Sanitizer with Vitamin E and Aloe Vera

Active Ingredients

Ethyl Alcohol 83%

Purpose

Antiseptic

Uses:

As a hand sanitizer to help reduce bacteria on the skin that potentially could cause disease. For use when soap and water are not available. Recommended for repeated use.

WARNINGS:

Flammable. Keep away from fire or flame.

For external use only.

When Using This Product:

In case of contact with eyes, rinse eyes throughly with water. Avoid contact with broken skin. Do not inhale or ingest.

Stop use and ask a doctor

if irritation or redness develops. Condition persists for more than 72 hours.

Keep out of reach of children.

If swallowed, get medical help or contact a Poison Control Center right away.

Directions

Wet hands thoroughly with product and allow to dry without wiping. For children under 6, use only under adult supervision. Not recommended for infants.

Other Information

Do not store above 105°F(41°C). May discolor some fabrics or surfaces.

Inactive Ingredients

Water, Amine, Carbomer, Glycerin, Aloe Barbadensis Leaf Juice (Aloe Vera), Tocopheryl Acetate (Vitamine E).